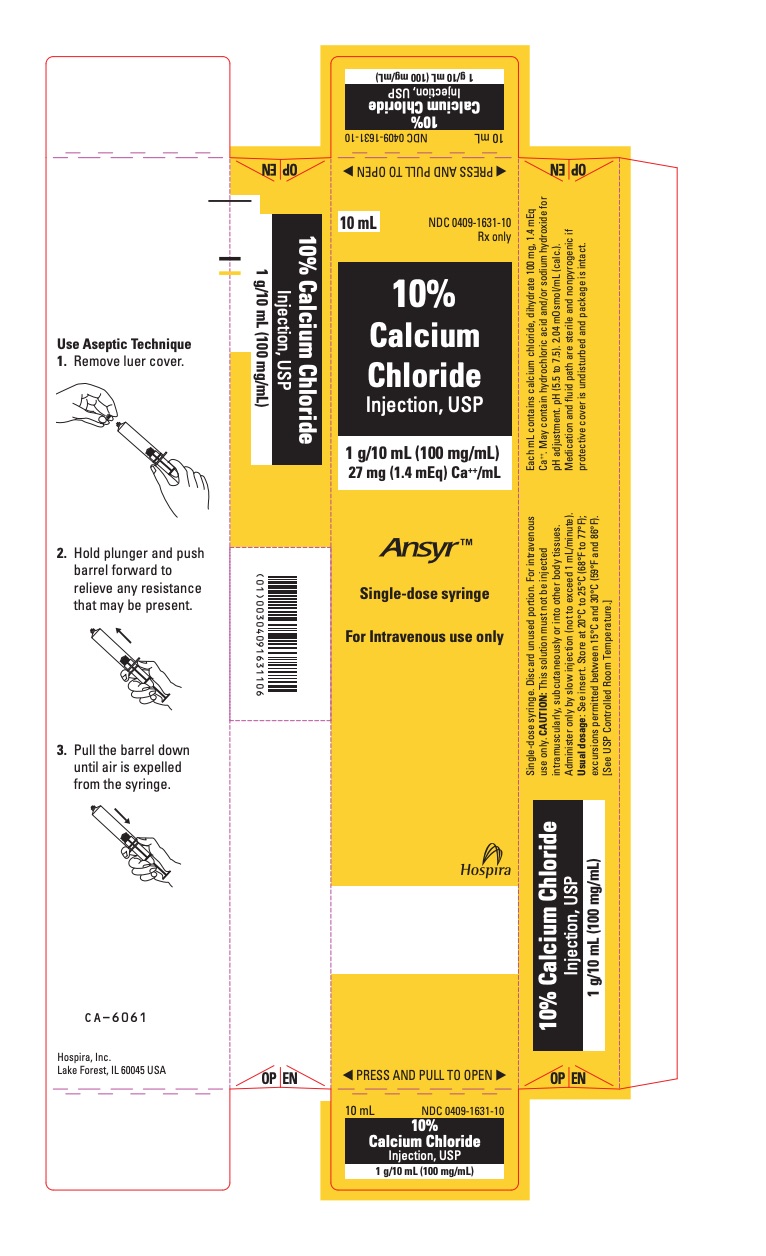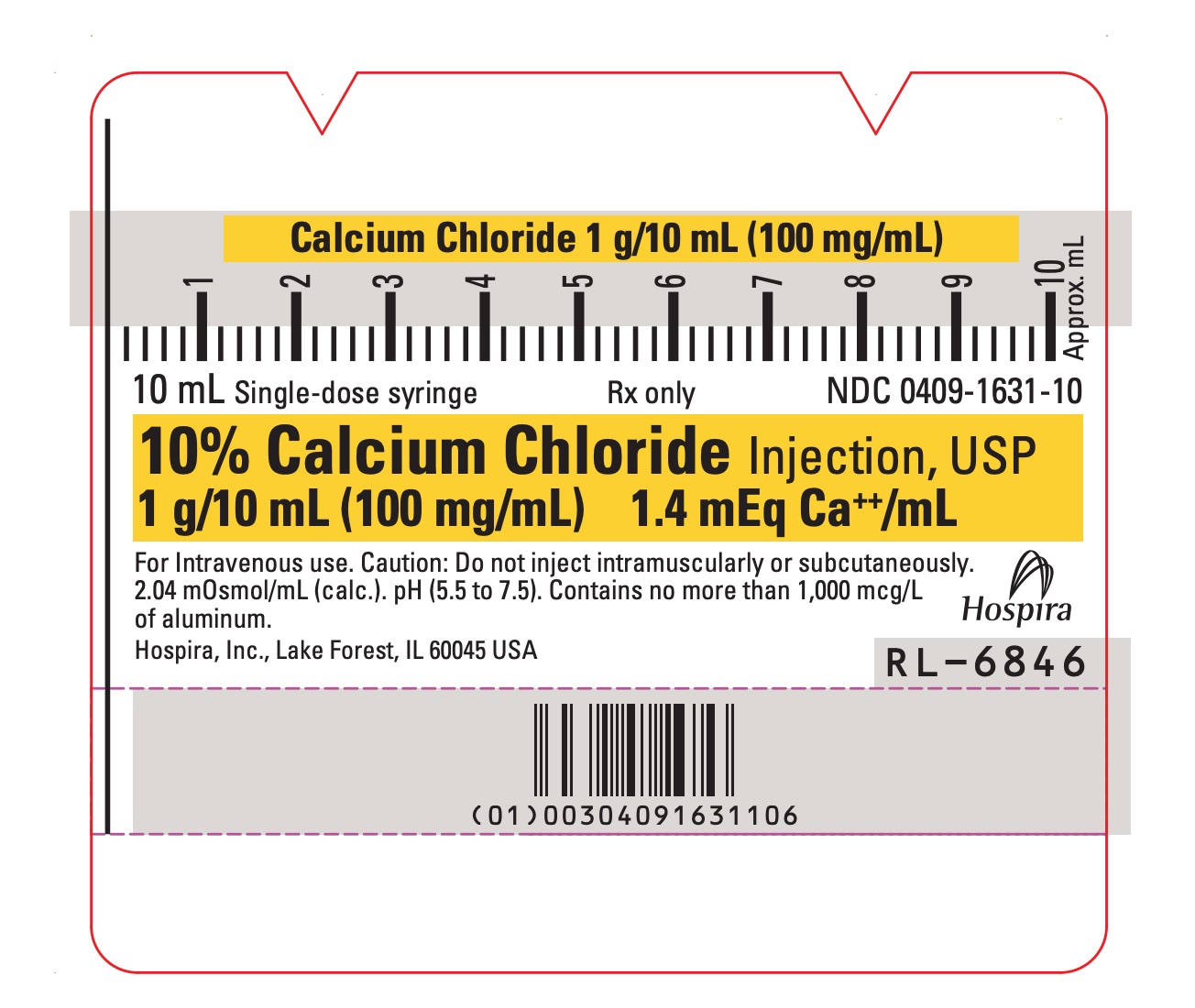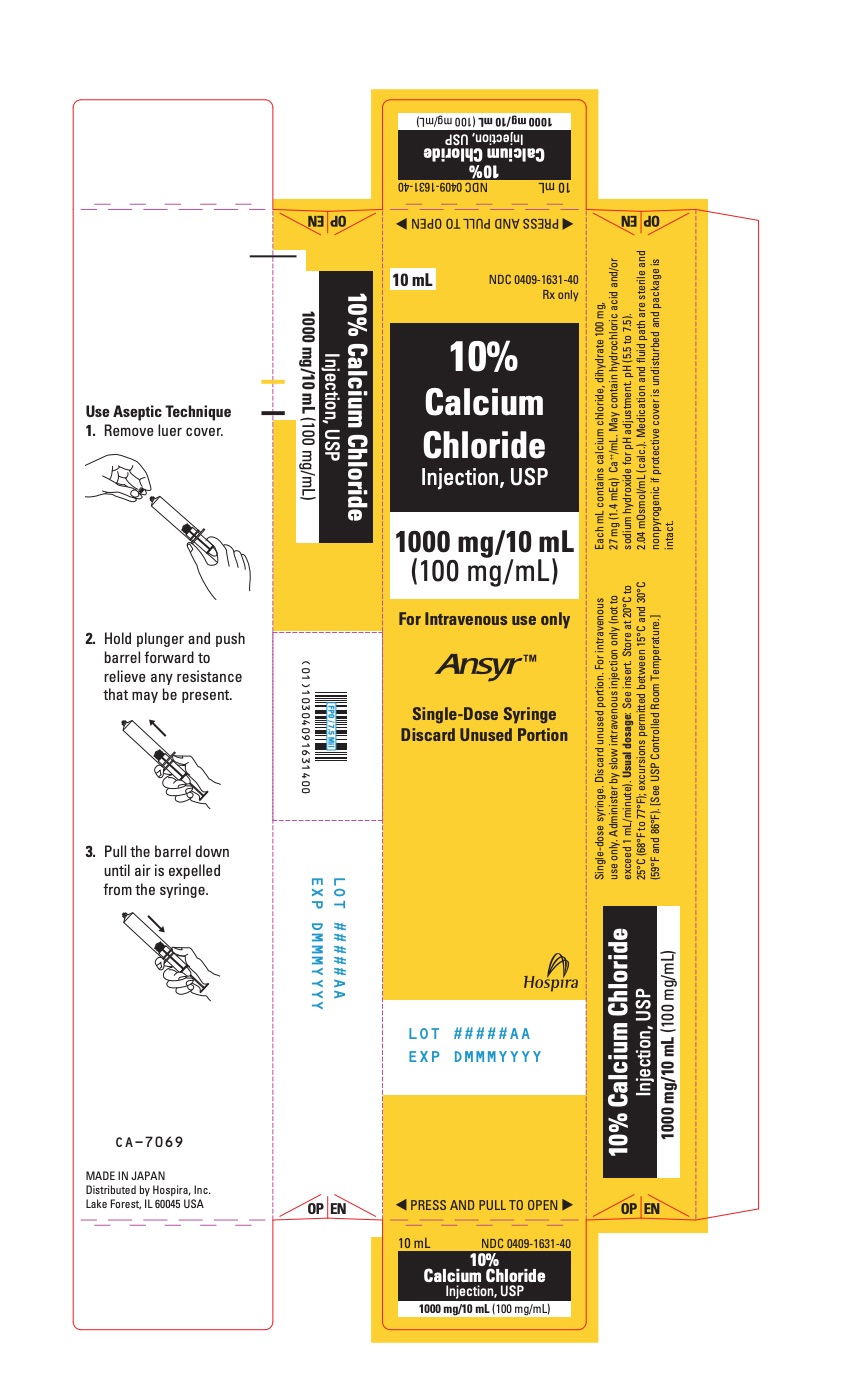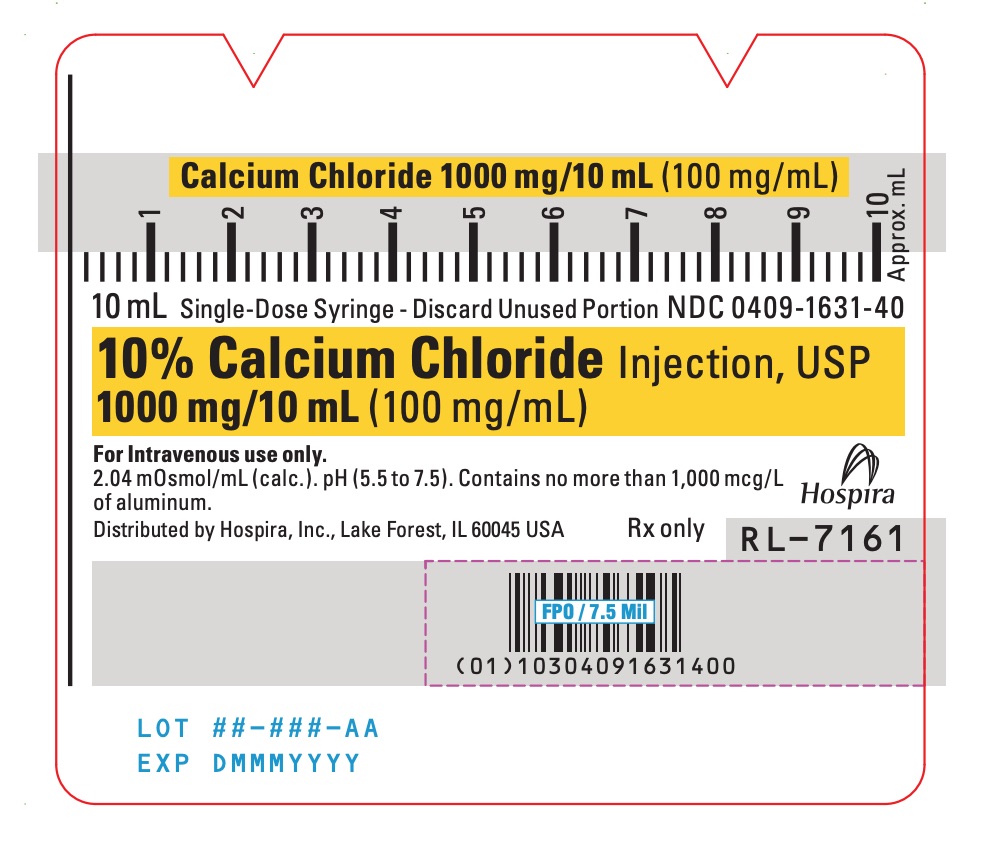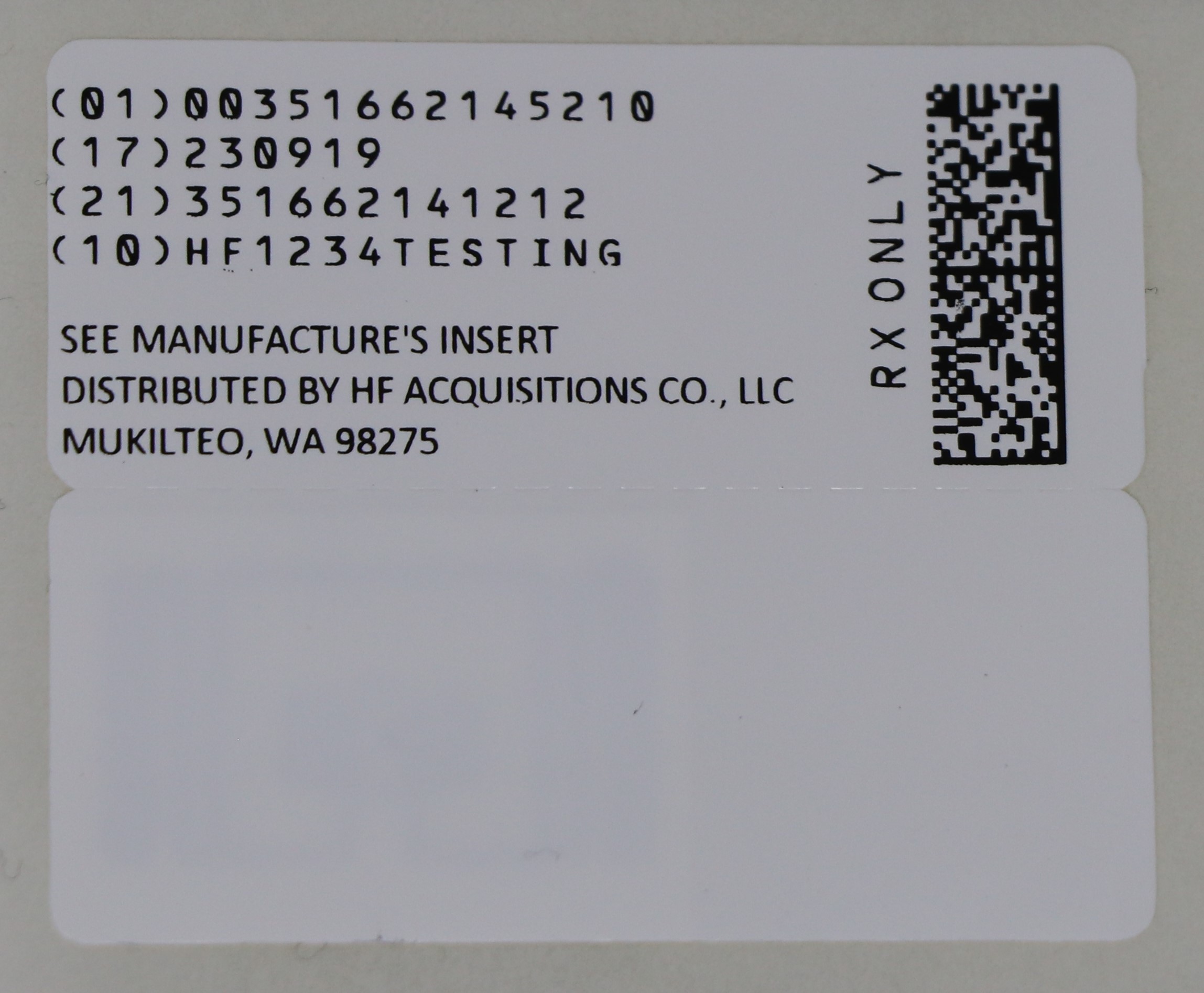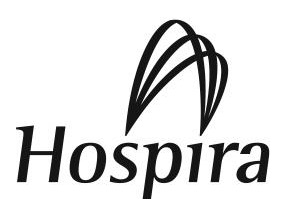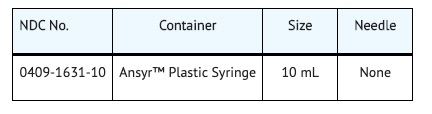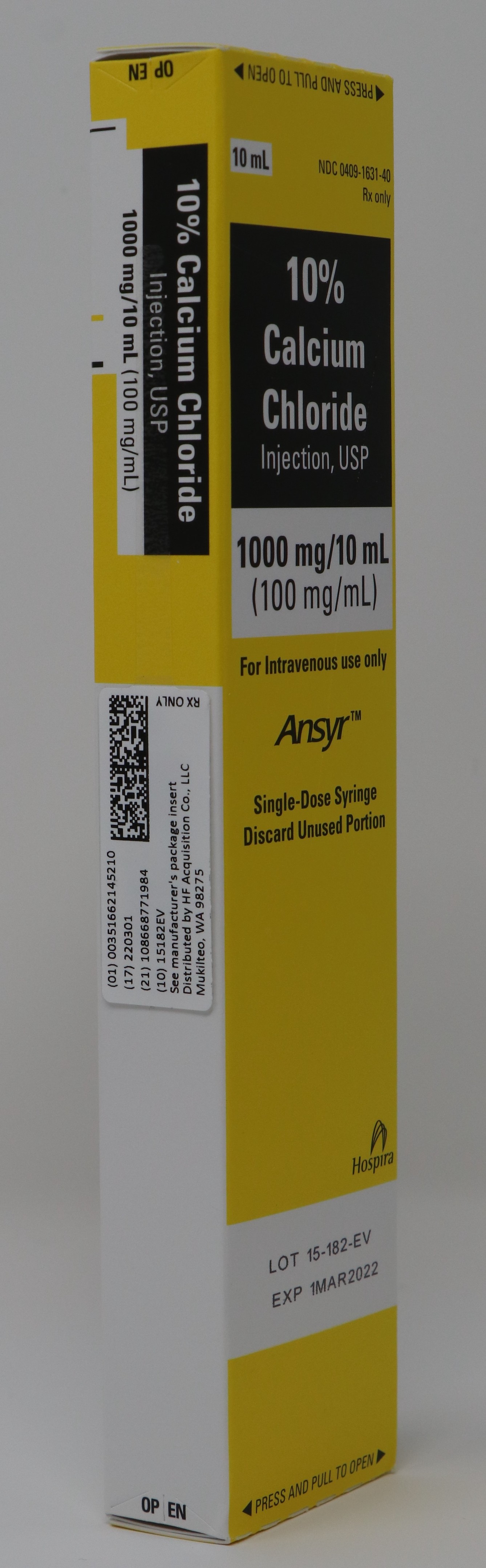 DRUG LABEL: CALCIUM CHLORIDE
NDC: 51662-1452 | Form: INJECTION, SOLUTION
Manufacturer: HF Acquisition Co LLC, DBA HealthFirst
Category: prescription | Type: HUMAN PRESCRIPTION DRUG LABEL
Date: 20240226

ACTIVE INGREDIENTS: CALCIUM CHLORIDE 100 mg/1 mL
INACTIVE INGREDIENTS: SODIUM HYDROXIDE; WATER; HYDROCHLORIC ACID

10% CALCIUM CHLORIDE INJECTION, USP 1000mg/10mL (100mg/mL) SYR

SPL UNCLASSIFIED

1 Gram (100 mg/mL)

Represents 27 mg (1.4 mEq) Ca++/mL

Ansyr™ Plastic Syringe

A HYPERTONIC SOLUTION IN A 10 ML UNIT OF USE SYRINGE FOR PROMPT INTRAVENOUS INJECTION.

CAUTION: This solution must not be injected intramuscularly or subcutaneously.

Administer only by slow injection

(not to exceed 1 mL/minute)

Rx only

DESCRIPTION

10% Calcium Chloride Injection, USP is a sterile, nonpyrogenic, hypertonic solution. Each mL contains 100 mg (1.4 mEq/mL) of calcium chloride, dihydrate (1.4 mEq each of Ca++ and Cl−) in water for injection. It is provided in a 10 mL Unit of Use Syringe to facilitate prompt intravenous injection. The solution contains no bacteriostat, antimicrobial agent or added buffer and is intended for use only as a single-dose injection. The pH of 10% Calcium Chloride Injection, USP is 5.5 to 7.5 when diluted with water for injection to make a 5% solution. May contain hydrochloric acid and/or sodium hydroxide for pH adjustment. The osmolar concentration is 2.04 mOsmol/mL (calc.). 10% Calcium Chloride Injection, USP is oxygen sensitive.

Calcium Chloride, USP dihydrate is chemically designated CaCl2 • 2H2O (dihydrate) and is described as white, odorless fragments or granules freely soluble in water.

The plastic syringe is molded from a specially formulated polypropylene. Water permeates from inside the container at an extremely slow rate which will have an insignificant effect on solution concentration over the expected shelf life. Solutions in contact with the plastic container may leach out certain chemical components from the plastic in very small amounts; however, biological testing was supportive of the safety of the syringe material.

CLINICAL PHARMACOLOGY

Calcium is the fifth most abundant element in the body and the major fraction is in the bony structure. Calcium plays important physiological roles, many of which are poorly understood. It is essential for the functional integrity of the nervous and muscular systems. It is necessary for normal cardiac function and is one of the factors that operates in the mechanisms involved in the coagulation of blood.

Calcium chloride in water dissociates to provide calcium (Ca++) and chloride (Cl−) ions. They are normal constituents of the body fluids and are dependent on various physiological mechanisms for maintenance of balance between intake and output. Approximately 80% of body calcium is excreted in the feces as insoluble salts; urinary excretion accounts for the remaining 20%.

CONTRAINDICATIONS

Calcium chloride is contraindicated for cardiac resuscitation in the presence of ventricular fibrillation or in patients with the risk of existing digitalis toxicity.

Calcium chloride is not recommended in the treatment of asystole and electromechanical dissociation.

WARNINGS

10% Calcium Chloride Injection, USP is irritating to veins and must not be injected into tissues, since severe necrosis and sloughing may occur. Great care should be taken to avoid extravasation or accidental injection into perivascular tissues.

WARNING: This product contains aluminum that may be toxic. Aluminum may reach toxic levels with prolonged parenteral administration if kidney function is impaired. Premature neonates are particularly at risk because their kidneys are immature, and they require large amounts of calcium and phosphate solutions, which contain aluminum.

Research indicates that patients with impaired kidney function, including premature neonates, who receive parenteral levels of aluminum at greater than 4 to 5 mcg/kg/day accumulate aluminum at levels associated with central nervous system and bone toxicity. Tissue loading may occur at even lower rates of administration.

PRECAUTIONS

Do not administer unless solution is clear and seal is intact. Discard unused portion.

Because of its additive effect, calcium should be administered very cautiously to a patient who is digitalized or who is taking effective doses of digitalis or digitalis-like preparations.

Injections should be made slowly through a small needle into a large vein to minimize venous irritation and avoid undesirable reactions. It is particularly important to prevent a high concentration of calcium from reaching the heart because of the danger of cardiac syncope.

Carcinogenesis, Mutagenesis, Impairment of Fertility:

Studies with solutions in polypropylene syringes have not been performed to evaluate carcinogenic potential, mutagenic potential or effects on fertility.

Pediatric Use:

Safety and effectiveness are based on similar clinical conditions in children and adults.

Pregnancy:

Animal reproduction studies have not been conducted with calcium chloride. It also is not known whether calcium chloride can cause fetal harm when administered to a pregnant woman or can affect reproductive capacity. Calcium chloride should be given to a pregnant woman only if clearly needed.

Geriatric Use:

An evaluation of current literature revealed no clinical experience identifying differences in response between elderly and younger patients. In general, dose selection for an elderly patient should be cautious, usually starting at the low end of the dosing range, reflecting the greater frequency of decreased hepatic, renal, or cardiac function, and of concomitant disease or other drug therapy.

ADVERSE REACTIONS

Rapid injection may cause the patient to complain of tingling sensations, a calcium taste, a sense of oppression or "heat wave".

Injections of calcium chloride are accompanied by peripheral vasodilatation as well as a local "burning" sensation and there may be a moderate fall in blood pressure.

Should perivascular infiltration occur, I.V. administration at that site should be discontinued at once. Local infiltration of the affected area with 1% procaine hydrochloride, to which hyaluronidase may be added, will often reduce venospasm and dilute the calcium remaining in the tissues locally. Local application of heat may also be helpful.

DRUG ABUSE

None known.

OVERDOSAGE

Too rapid injection may produce lowering of blood pressure and cardiac syncope. Persistent hypercalcemia from overdosage of calcium is unlikely because of rapid excretion. In the event of untoward effects from excessive calcium administration, the drug should be discontinued promptly, the patient re-evaluated and appropriate countermeasures instituted, if necessary. See PRECAUTIONS and ADVERSE REACTIONS.

DOSAGE & ADMINISTRATION

10% Calcium Chloride Injection, USP is administered only by slow intravenous injection (not to exceed 1 mL/min), preferably in a central or deep vein.

The usual precautions for intravenous therapy should be observed. If time permits, the solution should be warmed to body temperature. The injection should be halted if the patient complains of any discomfort; it may be resumed when symptoms disappear. Following injection, the patient should remain recumbent for a short time.

The usual adult dosage in hypocalcemic disorders ranges from 200 mg to 1 g (2 − 10 mL) at intervals of 1 to 3 days depending on the response of the patient and/or results of serum ionized calcium determinations. Repeated injections may be required because of rapid excretion of calcium.

The pediatric dosage in hypocalcemic disorders ranges from 2.7 to 5.0 mg/kg hydrated calcium chloride (or 0.136 to 0.252 mEq elemental calcium per kg, or 0.027 to 0.05 mL of 10% Calcium Chloride Injection per kg). No data from clinical trials is available about repeated dosages, though textbook references recommend repeat dosages q 4 to 6 hours.

Caution: 10% Calcium Chloride Injection consists of 1 gram of calcium chloride in a 10 mL syringe, or 100 mg/mL. This concentration represents 27 mg or 1.4 mEq of elemental calcium per mL. Thus, one 10 mL syringe provides 270 mg of elemental calcium. The dosage recommendation in various references is given either as amount of calcium chloride or amount of elemental calcium, and often it is not specified. Ionized calcium concentrations should be measured, to assist in dosage adjustment.

Parenteral drug products should be inspected visually for particulate matter and discoloration prior to administration, whenever solution and container permit. See PRECAUTIONS.

To prevent needle-stick injuries, needles should not be recapped, purposely bent or broken by hand.

HOW SUPPLIED

10% CALCIUM CHLORIDE INJECTION, USP is supplied in the following dosage forms:

NDC 51662-1452-1 10% CALCIUM CHLORIDE INJECTION, USP 1000mg/10mL (100mg/mL) SYR

HF Acquisition Co LLC, DBA HealthFirst
Mukilteo, WA 98275

Also supplied in the following manufacture supplied dosage forms

10% Calcium Chloride Injection, USP is supplied in single-dose containers as follows:

Store at 20 to 25°C (68 to 77°F). [See USP Controlled Room Temperature.]

CLINICAL STUDIES

Medical literature also refers to the administration of calcium chloride in the treatment of magnesium intoxication due to overdosage of magnesium sulfate, and to combat the deleterious effects of hyperkalemia as measured by electrocardiogram (ECG), pending correction of the increased potassium level in the extracellular fluid. However, adequate well-controlled, randomized clinical studies have not been done to support these indications.

SPL UNCLASSIFIED

Hospira, Inc., Lake Forest, IL 60045 USA

LAB-1022-2.0

Revised: 01/2018